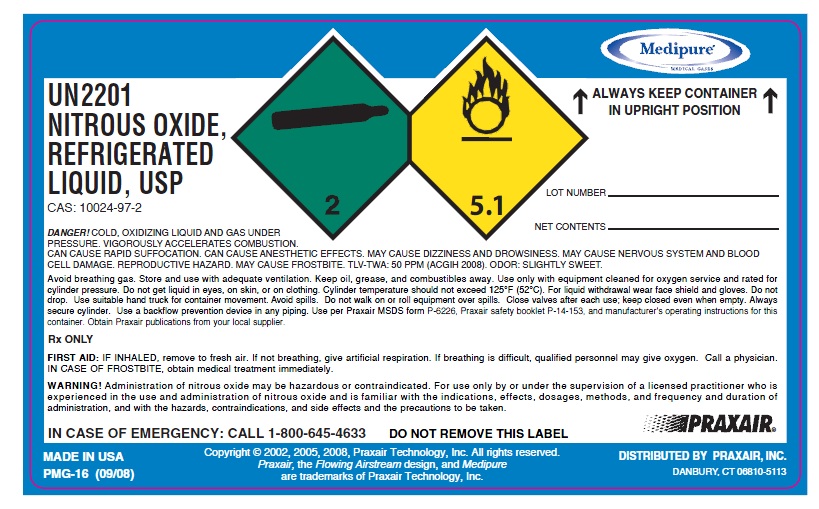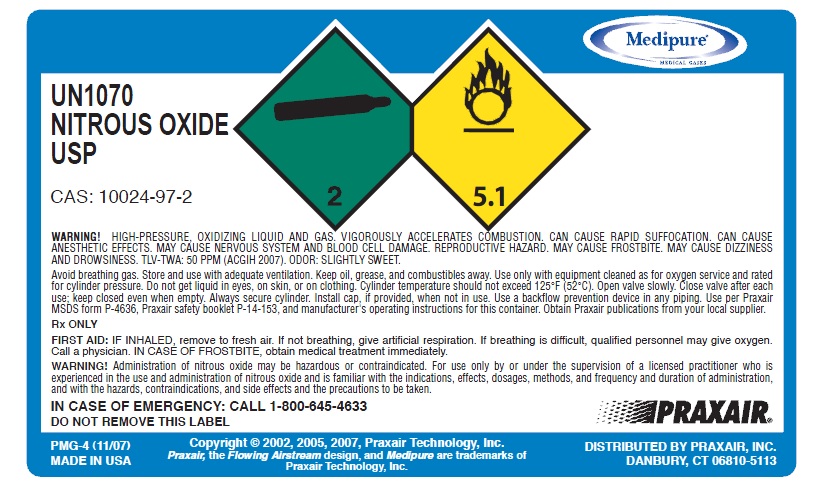 DRUG LABEL: Nitrous Oxide
NDC: 49972-004 | Form: GAS
Manufacturer: Praxair Distribution Southeast LLC
Category: prescription | Type: HUMAN PRESCRIPTION DRUG LABEL
Date: 20121203

ACTIVE INGREDIENTS: Nitrous Oxide 990 mL/1 L

Nitrous Oxide

PACKAGE LABEL

UN2201 NITROUS OXIDE, REFRIGERATED LIQUID, USP DANGER! COLD, OXIDIZING LIQUID AND GAS UNDER PRESSURE. VIGOROUSLY ACCELERATES COMBUSTION. CAN CAUSE RAPID SUFFOCATION. CAN CAUSE ANESTHETIC EFFECTS. MAY CAUSE DIZZINESS AND DROWSINESS. MAY CAUSE NERVOUS SYSTEM AND BLOOD CELL DAMAGE. REPRODUCTIVE HAZARD. MAY CAUSE FROSTBITE. TLV-TWA: 50 PPM (ACGIH 2008). ODOR: SLIGHTLY SWEET. Avoid breathing gas. Store and use with adequate ventilation. Keep oil, grease, and combustibles away. Use only with equipment cleaned for oxygen service and rated for cylinder pressure. Do not get liquid in eyes, on skin, or on clothing. Cylinder temperature should not exceed 125°F (52°C). For liquid withdrawal wear face shield and gloves. Do not drop. Use suitable hand truck for container movement. Avoid spills. Do not walk on or roll equipment over spills. Close valves after each use; keep closed even when empty. Always secure cylinder. Use a backflow prevention device in any piping. Use per Praxair MSDS form P-6226, Praxair safety booklet P-14-153, and manufacturer's operating instructions for this container. Obtain Praxair publications from your local supplier. Rx ONLY FIRST AID: IF INHALED, remove to fresh air. If not breathing, give artificial respiration. If breathing is difficult, qualified personnel may give oxygen. Call a physician. IN CASE OF FROSTBITE, obtain medical treatment immediately. WARNING! Administration of nitrous oxide may be hazardous or contraindicated. For use only by or under the supervision of a licensed practitioner who is experienced in the use and administration of nitrous oxide and is familiar with the indications, effects, dosages, methods, and frequency and duration of administration, and with the hazards, contraindications, and side effects and the precautions to be taken. DO NOT REMOVE THIS LABEL Rx ONLY CAS 10024-97-2 PRODUCED BY AIR LIQUEFACTION IN CASE OF EMERGENCY: CALL 1-800-645-4633 DISTRIBUTED BY PRAXAIR, INC., DANBURY PMG-16 (09/08) Copyright @ 2002, 2005, 2008. Praxair Technology, Inc. All rights reserved Praxair, the flowing airstream design and Medipure are trademarks of Praxair Technology, Inc. DISTRIBUTED BY PRAXAIR, INC, DANBURY, CT 06810-5113 DISTRIBUTED BY PRAXAIR, INC., DANBURY

PACKAGE LABEL

UN1070 NITROUS OXIDE USP CAS: 10024-97-2 CONTENTS LOT NUMBER WARNING! HIGH-PRESSURE OXIDIZING LIQUID AND GAS.VIGOROUSLY ACCELERATES COMBUSTION. CAN CAUSE RAPID SUFFOCATION.CAN CAUSE ANESTHETIC EFFECTS. MAY CAUSE NERVOUS SYSTEM AND BLOOD CELL DAMAGE. REPRODUCTIVE HAZARD. MAY CAUSE FROSTBITE MAY CAUSE DIZZINESS AND DROWSINESS. TLV-TWA: 50 PPM (ACGIH 2007) ODOR: SLIGHTLY SWEET. Avoid breathing gas. Store and use with adequate ventilation. Keep oil, grease, and combustibles away. Use only use with equipment cleaned as for oxygen service and rated for cylinder pressure. Do not get liquid in eyes, or on skin, or in clothing. Cylinder temperature should not exceed 125’F (52’C). Open valve slowly. Close valve after each use. Keep closed even when empty. Always secure cylinder. Install cap If provided, when not in use. Use backflow prevention device in any piping. Use per Praxair MSDS form P-4636. Praxair safety booklet P-14-153. And manufacturer’s operating instructions for this container. Obtain Praxair publications from your local supplier. Rx ONLY FIRST AID: IF INHALED, remove to fresh air. If not breathing, give artificial respiration. If breathing is difficult, qualified personnel may give oxygen. Call a physician. IN CASE OF FROSTBITE, obtain medical treatment immediately. WARNING! Administration of nitrous oxide may be hazardous or contraindicated, For use only by or under the supervision of a licensed practitioner who is experienced in the use and administration of nitrous oxide and is familiar with the indications, effects, dosages, methods, and frequency and duration of administration, and with the hazards, contraindications, and side effects and the precautions to be taken. IN CASE OF EMERGENCY: CALL 1-800-645-4633 DISTRIBUTED BY PRAXAIR, INC., DANBURY DO NOT REMOVE THIS LABEL PMG-4 (11/07) Copyright @ 2002, 2005, 2007, Praxair Technology, inc. Praxair, the flowing airstream design and Medipure are trademarks of Praxair Technology, Inc. DISTRIBUTED BY PRAXAIR, INC, DANBURY, CT 06810-5113 DISTRIBUTED BY PRAXAIR, INC., DANBURY